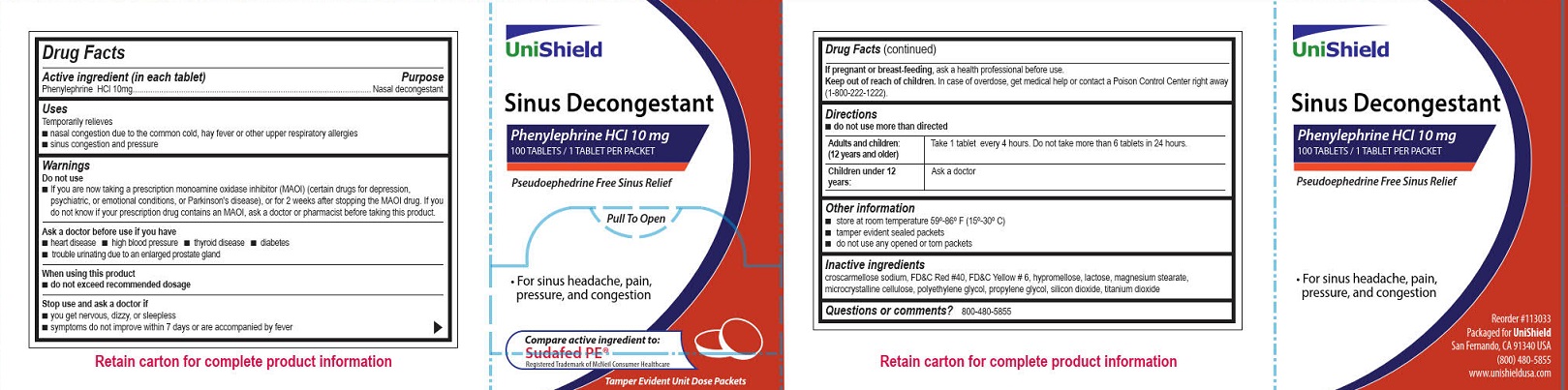 DRUG LABEL: Unishield Sinus Decongestant
NDC: 49314-2083 | Form: TABLET, FILM COATED
Manufacturer: Unishield
Category: otc | Type: HUMAN OTC DRUG LABEL
Date: 20250908

ACTIVE INGREDIENTS: PHENYLEPHRINE HYDROCHLORIDE 10 mg/1 1
INACTIVE INGREDIENTS: TITANIUM DIOXIDE; PROPYLENE GLYCOL; CROSCARMELLOSE SODIUM; FD&C RED NO. 40; HYPROMELLOSES; POLYETHYLENE GLYCOL, UNSPECIFIED; SILICON DIOXIDE; FD&C YELLOW NO. 6; LACTOSE, UNSPECIFIED FORM; CELLULOSE, MICROCRYSTALLINE; MAGNESIUM STEARATE

Unishield Sinus Decongestant

DRug Factr

Active ingredient (in each tablet)

Phenylephrine HCl 10 mg

Purpose

Nasal decongestant

INDICATIONS AND USAGE

Temporarily relieves

■ nasal congestion due to the common cold, hay fever or other upper respiratory allergies

■ sinus congestion and pressure

Warnings

Do not use

■ If you are now taking a prescription monoamine oxidase inhibitor (MAOI) (certain drugs for depression, psychiatric, or emotional conditions, or Parkinson's disease), or for 2 weeks after stopping the MAOI drug. If you do not know if your prescription drug contains an MAOI, ask a doctor or pharmacist before taking this product.

Ask a doctor before use if you have

■ heart disease

■ high blood pressure

■ thyroid disease

■ diabetes

■ trouble urinating due to an enlarged prostate gland

When using this product

■ do not exceed recommended dosage

Stop use and ask a doctor if

■ you get nervous, dizzy or sleepless

■ symptoms do not improve within 7 days or are accompanied by fever

PREGNANCY OR BREAST FEEDING

If pregnant or breast-feeding, ask a health professional before use.

Keep out of reach of children.

In case of overdose, get medical help or contact a Poison Control Center right away (1-800-222-1222).

Directions

■ do not use more than directed

Adults and children: (12 years and older) Take 1 tablet every 4 hours. Do not take more than 6 tablets in 24 hours.

Children under 12 years: Ask a doctor

Other information

■ store at room temperature 59º-86º F (15º-30º C)

■ tamper evident sealed packets

■ do not use any opened or torn packets

Inactive ingredients

croscarmellose sodium, FD&C red #40, FD&C yellow # 6, hypromellose, lactose, magnesium stearate, microcrystalline cellulose, polyethylene glycol, propylene glycol, silicon dioxide, titanium dioxide

Questions or comments? 800-480-5855

Unishield Sinus Decongestant Label

Unishield

Sinus Decongestant

Phenylephrine HCl 10 mg

100 Tablets/ 1 Tablet Per Packet

Pseudoephedrine Free Sinus Relief

Pull To Open

• For sinus headache, pain, pressure, and congestion

Compare active ingredients to:

Sudafed PE®

Registered Trademark of McNeil Consumer Healthcare

Tamper Evident Unit Dose Packets